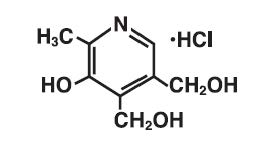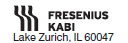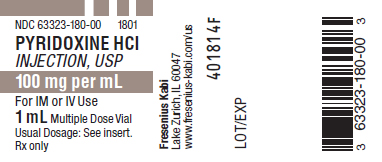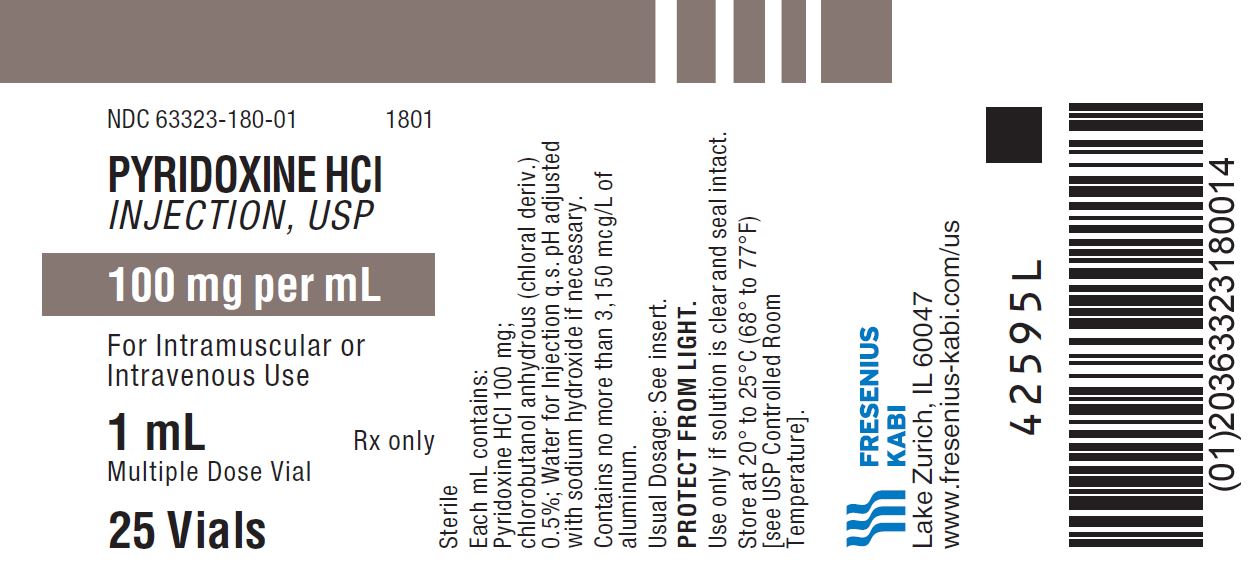 DRUG LABEL: Pyridoxine Hydrochloride
NDC: 63323-180 | Form: INJECTION, SOLUTION
Manufacturer: Fresenius Kabi USA, LLC
Category: prescription | Type: HUMAN PRESCRIPTION DRUG LABEL
Date: 20241015

ACTIVE INGREDIENTS: PYRIDOXINE HYDROCHLORIDE 100 mg/1 mL
INACTIVE INGREDIENTS: CHLOROBUTANOL 5 mg/1 mL; SODIUM HYDROXIDE

Pyridoxine Hydrochloride Injection, USP

100 mg per mL

DESCRIPTION:

Pyridoxine Hydrochloride Injection, USP is a sterile solution of pyridoxine hydrochloride in Water for Injection. Each mL contains 100 mg pyridoxine hydrochloride and 0.5% chlorobutanol anhydrous (chloral deriv.). pH adjusted with sodium hydroxide if necessary (2.0 to 3.8).

Pyridoxine hydrochloride is a colorless or white crystal or a white crystalline powder. One gram dissolves in 5 mL of water. It is stable in air and is slowly affected by sunlight.

The chemical name is 2-methyl-3-hydroxy-4,5-bis (hydroxymethyl) pyridine hydrochloride.

The structural formula is:

CLINICAL PHARMACOLOGY:

Natural substances that have vitamin B6 activity are pyridoxine in plants and pyridoxal or pyridoxamine in animals. All 3 are converted to pyridoxal phosphate by the enzyme pyridoxal kinase. The physiologically active forms of vitamin B6 are pyridoxal phosphate (codecarboxylase) and pyridoxamine phosphate. Riboflavin is required for the conversion of pyridoxine phosphate to pyridoxal phosphate.

Vitamin B6 acts as a coenzyme in the metabolism of protein, carbohydrate, and fat. In protein metabolism, it participates in the decarboxylation of amino acids, conversion of tryptophan to niacin or to serotonin (5-hydroxtryptamine), deamination, and transamination and transulfuration of amino acids. In carbohydrate metabolism, it is responsible for the breakdown of glycogen to glucose-1-phosphate.

The total adult body pool consists of 16 to 25 mg of pyridoxine. Its half-life appears to be 15 to 20 days. Vitamin B6 is degraded to 4-pyridoxic acid in the liver. This metabolite is excreted in the urine.

The need for pyridoxine increases with the amount of protein in the diet. The tryptophan load test appears to uncover early vitamin B6 deficiency by detecting xanthinurea. The average adult minimum daily requirement is about 1.25 mg. The ‘‘Recommended Dietary Allowance’’ of the National Academy of Sciences is estimated to be as much as 2.2 mg for adults and 2.5 mg for pregnant and lactating women. The requirements are more in persons having certain genetic defects or those being treated with isonicotinic acid hydrazide (INHJ) or oral contraceptives.

INDICATIONS AND USAGE:

Pyridoxine Hydrochloride Injection is effective for the treatment of pyridoxine deficiency as seen in the following:

Inadequate dietary intake.

Drug-induced deficiency, as from isoniazid (INH) or oral contraceptives.

Inborn errors of metabolism, e.g., vitamin B6 dependent convulsions or vitamin B6 responsive anemia.

The parenteral route is indicated when oral administration is not feasible as in anorexia, nausea and vomiting, and preoperative and postoperative conditions. It is also indicated when gastrointestinal absorption is impaired.

CONTRAINDICATIONS:

A history of sensitivity to pyridoxine or to any of the ingredients in Pyridoxine Hydrochloride Injection, USP is a contraindication.

WARNINGS:

WARNING: This product contains aluminum that may be toxic. Aluminum may reach toxic levels with prolonged parenteral administration if kidney function is impaired. Premature neonates are particularly at risk because their kidneys are immature, and they require large amounts of calcium and phosphate solutions, which contain aluminum.

Research indicates that patients with impaired kidney function, including premature neonates, who receive parenteral levels of aluminum at greater than 4 to 5 mcg/kg/day accumulate aluminum at levels associated with central nervous system and bone toxicity. Tissue loading may occur at even lower rates of administration.

PRECAUTIONS:

General

Single deficiency, as of pyridoxine alone, is rare. Multiple vitamin deficiency is to be expected in any inadequate diet. Patients treated with levodopa should avoid supplemental vitamins that contain more than 5 mg pyridoxine in the daily dose.

Women taking oral contraceptives may exhibit increased pyridoxine requirements.

Drug Interactions

Pyridoxine supplements should not be given to patients receiving levodopa, because the action of the latter drug is antagonized by pyridoxine. However, this vitamin may be used concurrently in patients receiving a preparation containing both carbidopa and levodopa.

Pregnancy

Pregnancy Category A—The requirement for pyridoxine appears to be increased during pregnancy. Pyridoxine is sometimes of value in the treatment of nausea and vomiting of pregnancy.

Nursing Mothers

The need for pyridoxine is increased during lactation. It is not known whether this drug is excreted in human milk. Because many drugs are excreted in human milk, caution should be exercised when pyridoxine hydrochloride is administered to a nursing woman.

Usage in Children

Safety and effectiveness in children have not been established.

ADVERSE REACTIONS:

To report SUSPECTED ADVERSE REACTIONS, contact Fresenius Kabi USA, LLC at 1-800-551-7176 or FDA at 1-800-FDA-1088 or www.fda.gov/medwatch.

Paresthesia, somnolence, and low serum folic acid levels have been reported.

DRUG ABUSE AND DEPENDENCE:

Symptoms of dependence have been noted in adults given only 200 mg daily, followed by withdrawal.

OVERDOSAGE:

Pyridoxine given to animals in amounts of 3 to 4 g/kg of body weight produces convulsions and death. In man, a dose of 25 mg/kg of body weight is well tolerated.

DOSAGE AND ADMINISTRATION:

Pyridoxine Hydrochloride Injection may be administered intramuscularly or intravenously. In cases of dietary deficiency, the dosage is 10 to 20 mg daily for 3 weeks. Follow-up treatment is recommended daily for several weeks with an oral therapeutic multivitamin preparation containing 2 to 5 mg pyridoxine. Poor dietary habits should be corrected, and an adequate, well balanced diet should be prescribed.

The vitamin B6 dependency syndrome may require a therapeutic dosage of as much as 600 mg a day and a daily intake of 30 mg for life.

In deficiencies due to INH, the dosage is 100 mg daily for 3 weeks followed by a 30 mg maintenance dose daily.

In poisoning caused by ingestion of more than 10 g of INH, an equal amount of pyridoxine should be given — 4 g intravenously followed by 1 g intramuscularly every 30 minutes.

Parenteral drug products should be inspected visually for particulate matter and discoloration prior to administration, whenever solution and container permit.

HOW SUPPLIED:

Pyridoxine Hydrochloride Injection, USP is supplied as:

Product Code | Unit of Sale | Strength | Each
1801 | NDC 63323-180-01 Unit of 25 | 100 mg per mL | NDC 63323-180-00 1 mL fill, in a 2 mL multiple dose vial

PROTECT FROM LIGHT.

Use only if solution is clear and seal intact.

Sterile.

Store at 20° to 25°C (68° to 77°F) [see USP Controlled Room Temperature].

www.fresenius-kabi.com/us

45817G

Revised: September 2019

PACKAGE LABEL

PACKAGE LABEL - PRINCIPAL DISPLAY - Pyridoxine HCl 1 mL Multiple Dose Vial Label

NDC 63323-180-00

1801

PYRIDOXINE HCl INJECTION, USP

100 mg per mL

For IM or IV Use

1 mL Multiple Dose Vial

Usual Dosage: See insert.

Rx only

PACKAGE LABEL

PACKAGE LABEL - PRINCIPAL DISPLAY - Pyridoxine HCl 1 mL Multiple Dose Vial Tray Label

NDC 63323-180-01

1801

PYRIDOXINE HCl INJECTION, USP

100 mg per mL

For Intramuscular or
Intravenous Use

1 mL Rx only
Multiple Dose Vial

25 Vials